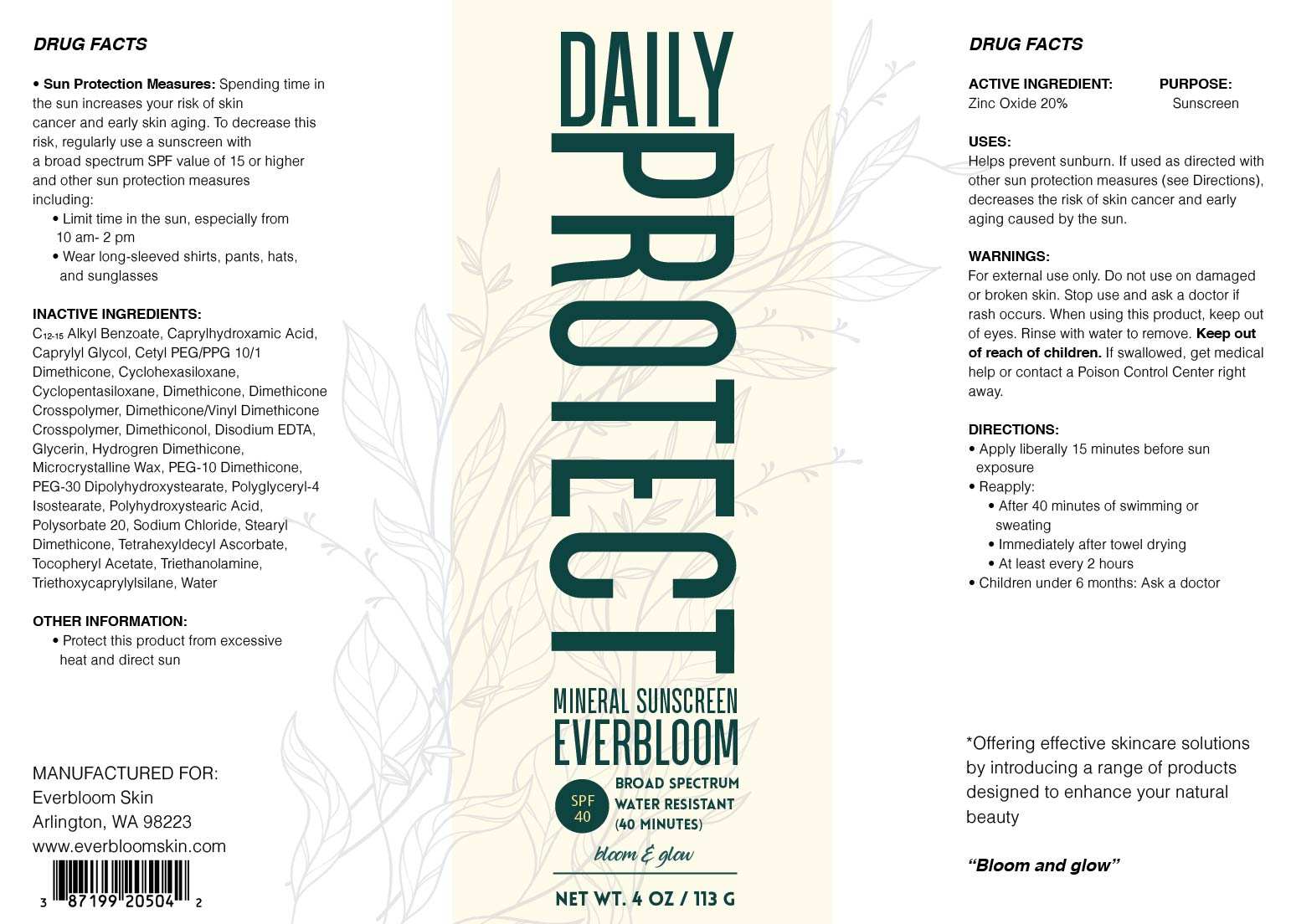 DRUG LABEL: Daily Protect Mineral Sunscreen
NDC: 87199-205 | Form: CREAM
Manufacturer: SARAH'S
Category: otc | Type: HUMAN OTC DRUG LABEL
Date: 20251216

ACTIVE INGREDIENTS: ZINC OXIDE 200 mg/1 g
INACTIVE INGREDIENTS: CYCLOHEXASILOXANE; HYDROGEN DIMETHICONE (20 CST); POLYGLYCERYL-4 ISOSTEARATE; STEARYL DIMETHICONE (400 MPA.S AT 50C); POLYSORBATE 20; TETRAHEXYLDECYL ASCORBATE; WATER; DIMETHICONE CROSSPOLYMER; C12-15 ALKYL BENZOATE; CAPRYLHYDROXAMIC ACID; CAPRYLYL GLYCOL; CYCLOPENTASILOXANE; DIMETHICONOL (2000 CST); EDETATE DISODIUM ANHYDROUS; GLYCERIN; PEG-10 DIMETHICONE (600 CST); POLYHYDROXYSTEARIC ACID (2300 MW); DIMETHICONE/VINYL DIMETHICONE CROSSPOLYMER (SOFT PARTICLE); TRIETHANOLAMINE; ALPHA-TOCOPHEROL ACETATE; DIMETHICONE; PEG-30 DIPOLYHYDROXYSTEARATE; CETYL PEG/PPG-10/1 DIMETHICONE (HLB 4); MICROCRYSTALLINE WAX; SODIUM CHLORIDE; TRIETHOXYCAPRYLYLSILANE

ACTIVE INGREDIENT

ZINC OXIDE 20%

PURPOSE

SUNSCREEN

USES

Helps Prevent Sunburn. If used as directed with other sun protection measures (see “Directions”), decreases the risk of skin cancer and early skin aging caused by the sun.

WARNINGS

For external use only. Do not use on broken or damaged skin. Stop use and ask a doctor if rash occurs. When using this product, keep out of eyes. Rinse with water to remove. Keep out of reach of children. If swallowed, get medical help or contact a poison control center right away.

WARNING

KEEP OUT OF REACH OF CHILDREN

DIRECTIONS

Apply liberally 15 minutes before sun exposure. Use a water-resistant product if swimming or sweating. Reapply at least every 2 hours. Children under 6 months: Ask a doctor. Sun Protection Measures: Spending time in the sun increases your risk of skin cancer and early skin aging. To decrease this risk, regularly use a sunscreen with a Broad-Spectrum SPF value of 15 or higher and other sun protection measures including: Limit time in the sun, especially from 10 a.m. - 2 p.m. Wear long-sleeved shirts, pants, hats and sunglasses.

INACTIVE INGREDIENTS

C12-15 Alkyl Benzoate, Caprylhydroxamic Acid, Caprylyl Glycol, Cetyl PEG/PPG-10/1 Dimethicone, Cyclohexasiloxane, Cyclopentasiloxane, Dimethicone, Dimethicone Crosspolymer, Dimethicone/Vinyl Dimethicone Crosspolymer, Dimethiconol, Disodium EDTA, Glycerin, Hydrogen Dimethicone, Microcrystalline Wax, PEG-10 Dimethicone, PEG-30 Dipolyhydroxystearate, Polyglyceryl-4 Isostearate, Polyhydroxystearic Acid, Polysorbate 20, Sodium Chloride, Stearyl Dimethicone, Tetrahexyldecyl Ascorbate, Tocopheryl Acetate, Triethanolamine, Triethoxycaprylylsilane, Water

OTHER SAFETY

- PROTECT THIS PRODUCT FROM EXCESSIVE HEAT AND DIRECT SUN